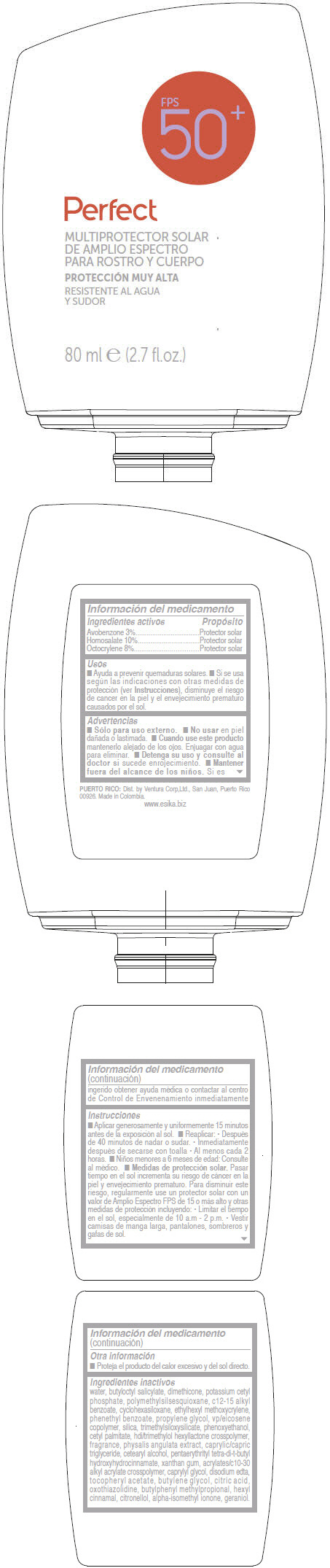 DRUG LABEL: ESIKA PERFECTBLOCK MULTIPROTECTOR SOLAR DE AMPLIO ESPECTRO PARA ROSTRO Y CUERPO FPS 50PLUS
NDC: 13537-988 | Form: LOTION
Manufacturer: Ventura Corporation LTD
Category: otc | Type: HUMAN OTC DRUG LABEL
Date: 20160714

ACTIVE INGREDIENTS: Avobenzone 0.03 g/1 mL; Homosalate 0.1 g/1 mL; Octocrylene 0.08 g/1 mL
INACTIVE INGREDIENTS: WATER; BUTYLOCTYL SALICYLATE; DIMETHICONE; POTASSIUM CETYL PHOSPHATE; ALKYL (C12-15) BENZOATE; CYCLOMETHICONE 6; ETHYLHEXYL METHOXYCRYLENE; PHENETHYL BENZOATE; PROPYLENE GLYCOL; SILICON DIOXIDE; PHENOXYETHANOL; CETYL PALMITATE; HEXAMETHYLENE DIISOCYANATE/TRIMETHYLOL HEXYLLACTONE CROSSPOLYMER; PHYSALIS ANGULATA; MEDIUM-CHAIN TRIGLYCERIDES; CETOSTEARYL ALCOHOL; PENTAERYTHRITOL TETRAKIS(3-(3,5-DI-TERT-BUTYL-4-HYDROXYPHENYL)PROPIONATE); XANTHAN GUM; CARBOMER INTERPOLYMER TYPE A (ALLYL SUCROSE CROSSLINKED); CAPRYLYL GLYCOL; EDETATE DISODIUM; .ALPHA.-TOCOPHEROL ACETATE; BUTYLENE GLYCOL; CITRIC ACID MONOHYDRATE; OXOTHIAZOLIDINE; BUTYLPHENYL METHYLPROPIONAL; .ALPHA.-HEXYLCINNAMALDEHYDE; .BETA.-CITRONELLOL, (R)-; ISOMETHYL-.ALPHA.-IONONE; GERANIOL

ESIKA PERFECTBLOCK MULTIPROTECTOR SOLAR DE AMPLIO ESPECTRO PARA ROSTRO Y CUERPO FPS 50+

Información del medicamento

ACTIVE INGREDIENT

PURPOSE

Ingredientes activos | Propósito
AVOBENZONE 3% | Protector solar
HOMOSALATE 10% | Protector solar
OCTOCRYLENE 8% | Protector solar

Usos

- Ayuda a prevenir quemaduras solares.
- Si se usa según las indicaciones con otras medidas de protección (ver Instrucciones), disminuye el riesgo de cancer en la piel y el envejecimiento prematuro causados por el sol.

Advertencias

- Sólo para uso externo.

DO NOT USE

- No usar en piel dañada o lastimada.

WHEN USING

- Cuando use este producto mantenerlo alejado de los ojos. Enjuagar con agua para eliminar.

STOP USE

- Detenga su uso y consulte al doctor si sucede enrojecimiento.

KEEP OUT OF REACH OF CHILDREN

- Mantener fuera del alcance de los niños. Si es ingerido obtener ayuda médica o contactar al centro de Control de Envenenamiento inmediatamente

Instrucciones

- Aplicar generosamente y uniformemente 15 minutos antes de la exposición al sol.
- Reaplicar:
  - Después de 40 minutos de nadar o sudar.
  - Inmediatamente después de secarse con toalla
  - Al menos cada 2 horas.
- Niños menores a 6 meses de edad: Consulte al médico
- Medidas de protección solar. Pasar tiempo en el sol incrementa su riesgo de cáncer en la piel y envejecimiento prematuro. Para disminuir este riesgo, regularmente use un protector solar con un valor de Amplio Espectro FPS de 15 o más alto y otras medidas de protección incluyendo:
  - Limitar el tiempo en el sol, especialmente de 10 a.m - 2 p.m.
  - Vestir camisas de manga larga, pantalones, sombreros y gafas de sol.

Otra información

- Proteja el producto del calor excesivo y del sol directo.

Ingredientes inactivos

WATER, BUTYLOCTYL SALICYLATE, DIMETHICONE, POTASSIUM CETYL PHOSPHATE, POLYMETHYLSILSESQUIOXANE, C12-15 ALKYL BENZOATE, CYCLOHEXASILOXANE, ETHYLHEXYL METHOXYCRYLENE, PHENETHYL BENZOATE, PROPYLENE GLYCOL, VP/EICOSENE COPOLYMER, SILICA, TRIMETHYLSILOXYSILICATE, PHENOXYETHANOL, CETYL PALMITATE, HDI/TRIMETHYLOL HEXYLLACTONE CROSSPOLYMER, FRAGRANCE, PHYSALIS ANGULATA EXTRACT, CAPRYLIC/CAPRIC TRIGLYCERIDE, CETEARYL ALCOHOL, PENTAERYTHRITYL TETRA-DI-t-BUTYL HYDROXYHYDROCINNAMATE, XANTHAN GUM, ACRYLATES/C10-30 ALKYL ACRYLATE CROSSPOLYMER, CAPRYLYL GLYCOL, DISODIUM EDTA, TOCOPHERYL ACETATE, BUTYLENE GLYCOL, CITRIC ACID, OXOTHIAZOLIDINE, BUTYLPHENYL METHYLPROPIONAL, HEXYL CINNAMAL, CITRONELLOL, ALPHA-ISOMETHYL IONONE, GERANIOL.

Dist. by Ventura Corp,Ltd., San Juan, Puerto Rico
00926.

PRINCIPAL DISPLAY PANEL - 80 ml Bottle Label

FPS
50^+

Perfect

MULTIPROTECTOR SOLAR
DE AMPLIO ESPECTRO
PARA ROSTRO Y CUERPO

PROTECCIÓN MUY ALTA

RESISTENTE AL AGUA
Y SUDOR

80 ml e (2.7 fl.oz.)